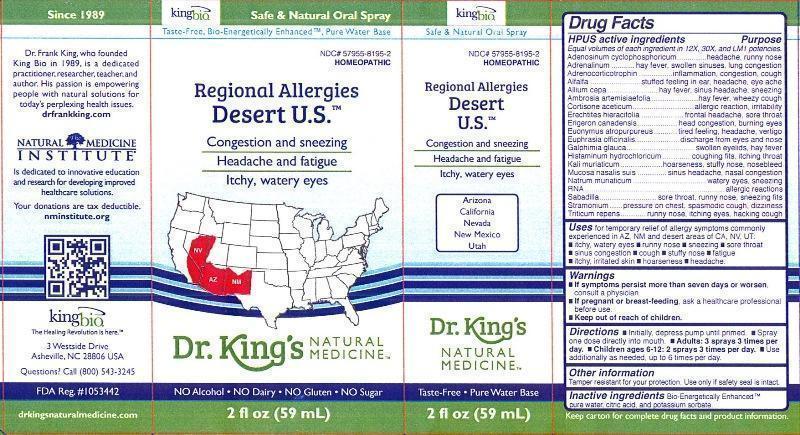 DRUG LABEL: Regional Allergies Desert U.S.
NDC: 57955-8195 | Form: LIQUID
Manufacturer: King Bio Inc.
Category: homeopathic | Type: HUMAN OTC DRUG LABEL
Date: 20130723

ACTIVE INGREDIENTS: ADENOSINE CYCLIC PHOSPHATE 12 [hp_X]/59 mL; EPINEPHRINE 12 [hp_X]/59 mL; CORTICOTROPIN 12 [hp_X]/59 mL; ALFALFA 12 [hp_X]/59 mL; ONION 12 [hp_X]/59 mL; AMBROSIA ARTEMISIIFOLIA 12 [hp_X]/59 mL; CORTISONE ACETATE 12 [hp_X]/59 mL; ERECHTITES HIERACIIFOLIUS 12 [hp_X]/59 mL; CONYZA CANADENSIS 12 [hp_X]/59 mL; EUONYMUS ATROPURPUREUS BRANCH BARK/ROOT BARK 12 [hp_X]/59 mL; EUPHRASIA STRICTA 12 [hp_X]/59 mL; GALPHIMIA GLAUCA FLOWERING TOP 12 [hp_X]/59 mL; HISTAMINE DIHYDROCHLORIDE 12 [hp_X]/59 mL; POTASSIUM CHLORIDE 12 [hp_X]/59 mL; SUS SCROFA NASAL MUCOSA 12 [hp_X]/59 mL; SODIUM CHLORIDE 12 [hp_X]/59 mL; SACCHAROMYCES CEREVISIAE RNA 12 [hp_X]/59 mL; SCHOENOCAULON OFFICINALE SEED 12 [hp_X]/59 mL; DATURA STRAMONIUM 12 [hp_X]/59 mL; ELYMUS REPENS ROOT 12 [hp_X]/59 mL
INACTIVE INGREDIENTS: WATER; CITRIC ACID MONOHYDRATE; POTASSIUM SORBATE

Regional Allergies Desert U.S.

ACTIVE INGREDIENT

Drug Facts___________________________________________________________________________________________________________

HPUS active ingredients: Adenosinum cyclophosphoricum, Adrenalinum, Adrenocorticotrophin, Alfalfa, Allium cepa, Ambrosia artemisiaefolia, Cortisone aceticum, Erechtites hieracifolia, Erigeron canadensis, Euonymus atropurpureus, Euphrasia officinalis, Galphimia glauca, Histaminum hydrochloricum, Kali muriaticum, Mucosa nasalis suis, Natrum muriaticum, RNA, Sabadilla, Stramonium and Triticum repens.

INDICATIONS AND USAGE

Uses for temporary relief of allergy symptoms commonly experienced in AZ, NM and desert areas of CA, NV, UT.

- itchy, watery eyes
- runny nose
- sneezing
- sore throat
- sinus congestion
- cough
- stuff nose
- fatigue
- itchy, irritated skin
- hoarseness
- headache

Warnings

- If symptoms persist more than seven days or worsen, consult a physician.
- If pregnant or breast-feeding, ask a healthcare professional before use.

Keep out of reach of children.

Directions

- Initially depress pump until primed.
- Spray one dose directly into mouth.
- Adults: 3 sprays 3 times per day.
- Children ages 6-12: 2 sprays 3 times per day.
- Use additionally as needed, up to 6 times per day.

Other information

Tamper resistant for your protection. Use only if safety seal is intact.

INACTIVE INGREDIENT

Inactive ingredients: Bio-Energetically Enhanced™ pure water, citric acid and potassium sorbate.

PURPOSE

Drug Facts___________________________________________________________________________________________________________

HPUS active ingredients Purpose

Equal volumes of each ingredient in 12X, 30X, and LM1 potencies.

Adenosinum cyclophosphoricum.........................................headache, runny nose

Adrenalinum....................................................................hay fever, swollen sinuses, lung congestion

Adrenocorticorticotrophin..................................................inflammation, congestion, cough

Alfalfa............................................................................stuffed feeling in ear, headache, eye ache

Allium cepa.....................................................................hay fever, sinus headache, sneezing

Ambrosia artemisiaefolia...................................................hay fever, wheezy cough

Cortisone aceticum...........................................................allergic reaction, irritability

Erechtites hieracifolia........................................................frontal headache, sore throat

Erigeron canadensis..........................................................head congestion, burning eyes

Euonymus atropurpureus...................................................tired feeling, headache, vertigo

Euphrasia officinalis...........................................................discharge from eyes and nose

Galphimia glauca...............................................................swollen eyelids, hay fever

Histaminum hydrochloricum................................................coughing fits, itching throat

Kali muriaticum.................................................................hoarseness, stuffy nose, nosebleed

Mucosa nasalis suis............................................................sinus headache, nasal congestion

Natrum muriaticum............................................................watery eyes, sneezing

RNA.................................................................................allergic reactions

Sabadilla..........................................................................sore throat, runny nose, sneezing fits

Stramonium......................................................................pressure on chest, spasmodic cough, dizziness

Triticum repens..................................................................runny nose, itching eyes, hacking cough